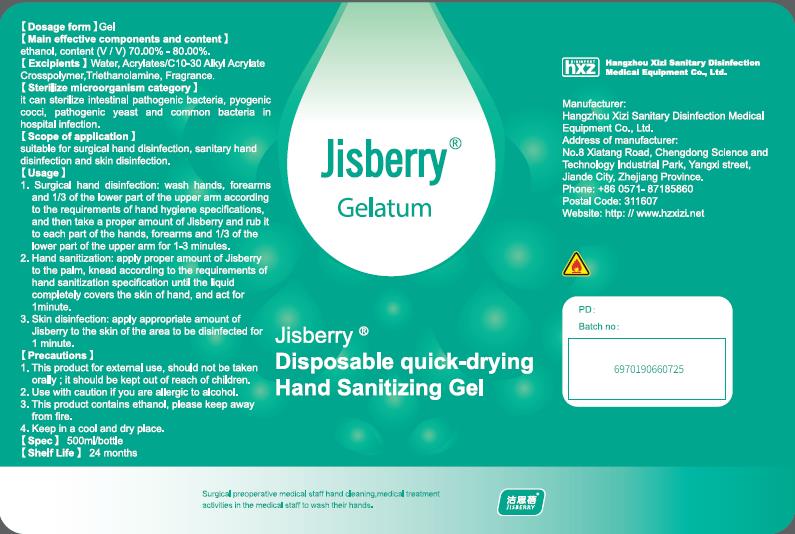 DRUG LABEL: Jisberry Disposabie  Quick-drying Hand Sanitizing
NDC: 52738-003 | Form: GEL
Manufacturer: Hangzhou Xizi Sanitary Disinfection Medical Equipment Co., Ltd
Category: otc | Type: HUMAN OTC DRUG LABEL
Date: 20200414

ACTIVE INGREDIENTS: ALCOHOL 350 mL/500 mL
INACTIVE INGREDIENTS: FRAGRANCE LAVENDER & CHIA F-153480; CARBOMER INTERPOLYMER TYPE A (55000 CPS); CUPRIC BIS(TRIETHANOLAMINE)

DOSAGE AND ADMINISTRATION

This product contains ethanol, please keep away from fire. Keep in a cool and dry place.

INACTIVE INGREDIENT

Water,

Acrylates/C10-30 Alkyl Acrylate Crosspolymer

Triethanolamine

Fragrance

INDICATIONS AND USAGE

1. Surgical hand disinfection: wash hands,forearms and 1/3 of the lower part of the upper arm according to the requirements of hand hygiene specifications, and then take a proper amount of Jisberry and rub it to each part of the hands, forearms and 1/3 of the lower part of the upper arm for 1-3 minutes.

2. Hand sanitization: apply proper amount of Jisberry to the palm,knead according to the requirements of hand sanitization specification until the liquid completely covers the skin of hand, and act for 1minute.

3. Skin disinfection: apply appropriate amount of Jisberry to the skin of the area to be disinfected for 1 minute.

ACTIVE INGREDIENT

Ethyl alcohol

keep out of children

PURPOSE

Disinfection
Sterilization
No Rinseing

WARNINGS

1. This product for external use, should not be taken orally ; it should be kept out of reach of children

2. Use with caution if you are allergic to alcohol.

3. This product contains ethanol, please keep away from fire.

4. Keep in a cool and dry place.